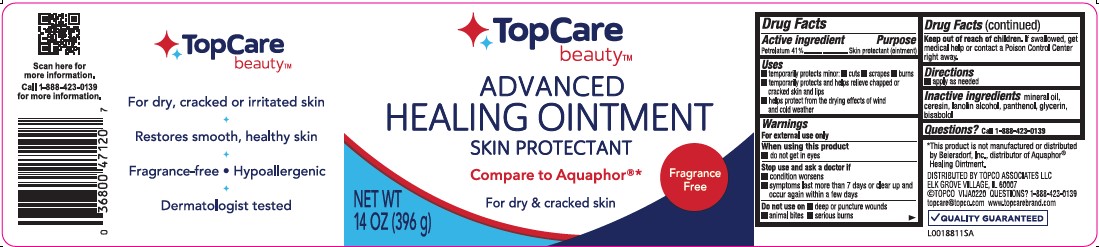 DRUG LABEL: Healing
NDC: 36800-247 | Form: OINTMENT
Manufacturer: Topco Associates LLC
Category: otc | Type: HUMAN OTC DRUG LABEL
Date: 20260213

ACTIVE INGREDIENTS: PETROLATUM 410 mg/1 g
INACTIVE INGREDIENTS: CERESIN; LANOLIN ALCOHOLS; PANTHENOL; GLYCERIN; LEVOMENOL; MINERAL OIL

Top Care 247.000/247AA-AC
Healing Ointment for Dry and Cracked Skin

Active ingredient

Petrolatum 41%

Purpose

Skin protectant (ointment)

Uses

- temporarily protects minor: cuts, scrapes, burns
- temporarily protects and helps relieve chapped or cracked skin and lips
- helps protects from the drying effects of wind and cold weather

Warnings

For external use only

When using this product

- do not get in eyes

Stop use and ask a doctor if

- condition worsens
- symptoms last more than 7 days or clear up and occur again within a few days

Do not use on

- deep or puncture wounds
- animal bites
- serious burns

Keep out of reach of children.

If swallowed, get medial help or contact a Poison Control Center right away.

Directions

- apply as needed

Inactive ingredients

mineral oil, ceresin, lanolin alcohol, panthenol, glycerin, bisabolol

Questions?

Call 1-888-423-0139

Claims

TopCare beauty™

For dry, cracked or irritated skin

Restores smooth, healthy skin

Fragrance-free Hypoallergenic

Dermatologist tested

ADVERSE REACTION

*This product is not manufactured or distributed by Beiersdorf, Inc., distributor of Aquaphor® Healing Ointment.

DISTRIBUTED BY TOPCO ASSOCIATES LLC

ELK GROVE VILLAGE, IL 60007

(C) TOPCO VIJA0220 QUESTIONS? 1-888-423-0139

topcare@topco.com www.topcarebrand.com

QUALITY GUARANTEED

Scan here for more information.

Call 1-888-423-0139 for more information.

principal display panel

TopCare

beauty™

ADVANCED

HEALING OINTMENT

SKIN PROTECTANT

Compare to Aquaphor®*

For dry & cracked skin

Fragrance Free

NET WT 14 OZ (396 g)